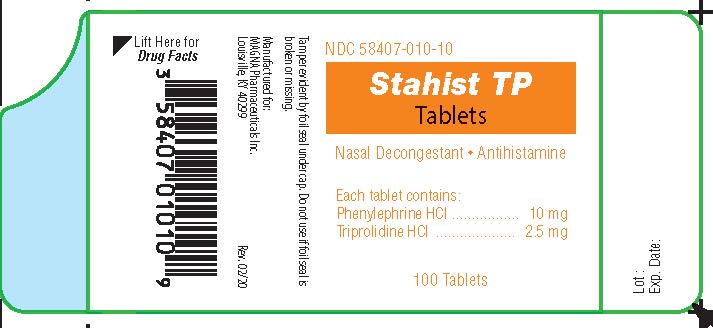 DRUG LABEL: STAHIST TP
NDC: 58407-010 | Form: TABLET
Manufacturer: Magna Pharmaceuticals, Inc.
Category: otc | Type: HUMAN OTC DRUG LABEL
Date: 20231010

ACTIVE INGREDIENTS: TRIPROLIDINE HYDROCHLORIDE 2.5 mg/1 1; PHENYLEPHRINE HYDROCHLORIDE 10 mg/1 1
INACTIVE INGREDIENTS: MAGNESIUM STEARATE; MICROCRYSTALLINE CELLULOSE; SODIUM STARCH GLYCOLATE TYPE A POTATO

Stahist TP

Drug Facts

Uses

temporarily relieves these symptoms due to the common cold, hay fever (allergic rhinitis) or other upper respiratory allergies:

- runny nose
- sneezing
- itching of the nose or throat
- itchy, watery eyes
- nasal congestion
- reduces swelling of nasal passages

Warnings

Do not exceed recommended dosage.

Do not use this product

- If you are taking a prescription monoamine oxidase inhibitor (MAOI) (certain drugs for depression, psychiatric, or emotional conditions, or Parkinson's disease), or for two weeks after stopping the MAOI drug. If you do not know if your prescription drug contains MAOI, ask a doctor or pharmacist before taking this product.

Ask a doctor before use if you have

- a breathing problem such as emphysema or chronic bronchitis
- glaucoma
- heart disease
- high blood pressure
- thyroid disease
- diabetes melitus
- difficulty in urination due to enlargement of the prostate gland

Ask a doctor before use if you are taking sedatives or tranquilizers

When using this product

- excitability may occur, especially in children
- may cause drowsiness
- alcohol, sedatives and tranquilizers may increase drowsiness effect
- avoid alcoholic beverages
- use caution when driving a motor vehicle or operating machinery

Stop use and ask a doctor if

- nervousness, dizziness or sleeplessness occur
- cough or nasal congestion persists for more than
  1 week, tends to recur or is accompanied by a fever, rash
  or persistent headache. These could be signs of a serious
  condition.
- new symptoms occur

PREGNANCY OR BREAST FEEDING

If pregnant or breast-feeding,ask a health professional before use.

Keep out of reach of children.

In case of accidental overdose, seek professional help or contact a Poison Control Center immediately.

Purpose

Nasal Decongestant

Antihistamine

Active Ingredients

(in each tablet)
Phenylephrine HCl 10 mg ..................... Nasal Decongestant
Triprolidine HCl 2.5 mg .................................. Antihistamine

Directions

Do not exceed recommended dosage.

Adults and children 12 years of age and over: | 1 tablet by mouth every 4 hours, not to exceed 4 tablets in 24 hours, or as directed by a doctor
Children 6 to under 12 years of age: | ½ tablet by mouth every 4 hours, not to exceed 2 tablets in 24 hours, or as directed by a doctor
Children under 6 years of age | Consult a doctor

Inactive ingredients

Magnesium Stearate, Microcrystalline Cellulose, Sodium Starch Glycolate

Questions or Comments?

Call 1-888-206-5525

Other Information

Store at 15°-30° C (59°-86° F)
Tamper evident by foil seal under cap. Do not use if foil seal is
missing or broken.

Rev. 2/20

PACKAGE LABEL

Add image transcription here...